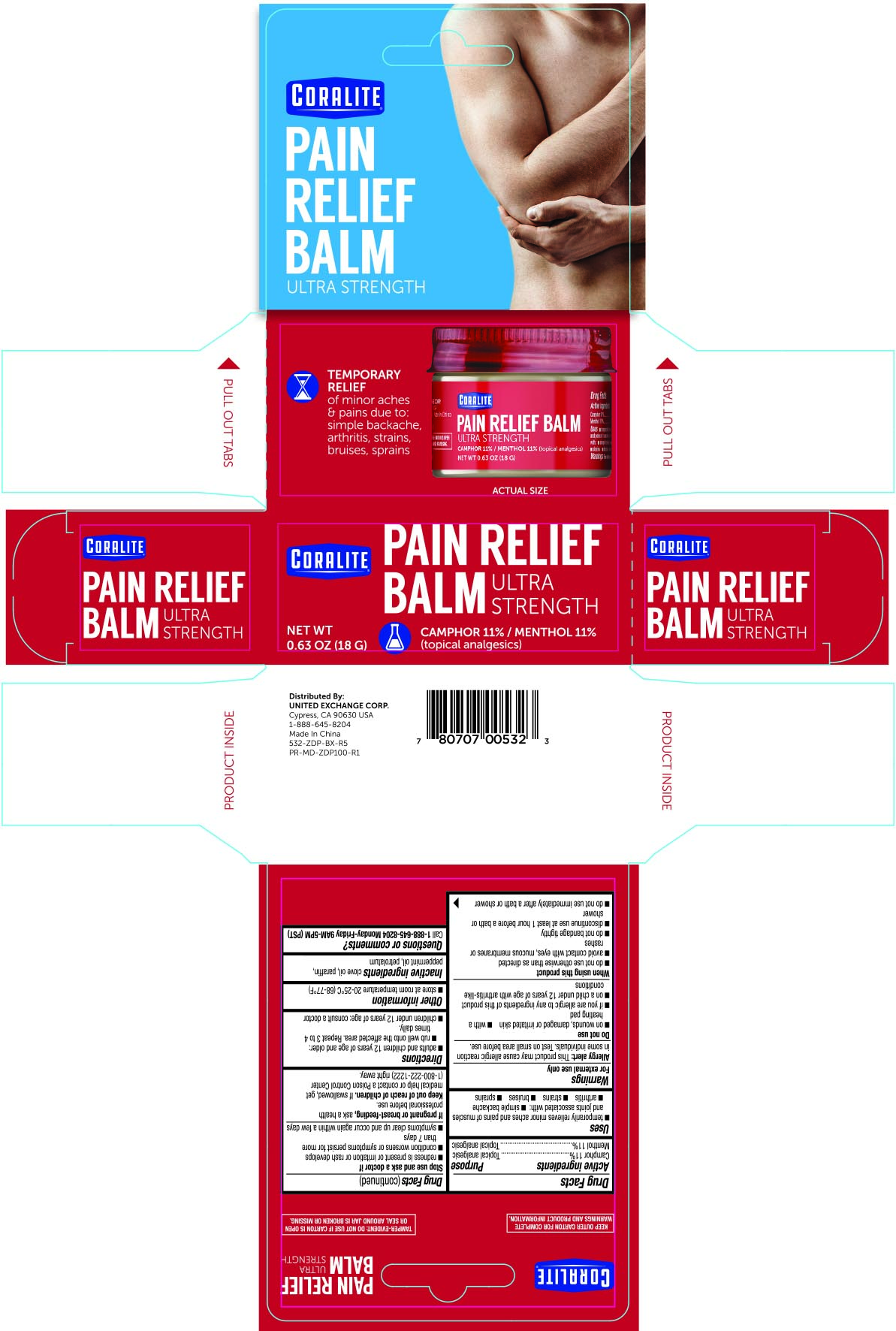 DRUG LABEL: Coralite Ultra Strength Pain Relief
NDC: 65923-532 | Form: OINTMENT
Manufacturer: United Exchange Corp.
Category: otc | Type: HUMAN OTC DRUG LABEL
Date: 20251029

ACTIVE INGREDIENTS: CAMPHOR (SYNTHETIC) 110 mg/1 g; MENTHOL 110 mg/1 g
INACTIVE INGREDIENTS: PEPPERMINT OIL; CLOVE OIL; PETROLATUM; PARAFFIN

Coralite Ultra Strength Pain Relief Balm 0.63oz (532)

Active ingredients Purpose

Camphor 11%........................................................ Topical analgesic

Menthol 11%.......................................................... Topical analgesic

Uses

- temporarily relieves minor aches and pains of muscles and joints associated with
- simple backache
- arthritis
- strains
- bruise
- sprains

Warnings

For external use only

Allergy alert: This product may cause allergic reaction in some individuals. Test on small area before use.

Do not use

- on wounds, damaged or irritated skin
- with a heating pad
- if you are allergic to any ingredients of this product
- on a child under 12 years of age with arthritis-like conditions

When using this product

- do not use otherwise than as directed
- avoid contact with the eyes, mucous membranes or rashes
- do not bandage tightly
- discontinue use at least 1 hour before a bath or shower
- do not use immediately after a bath or shower

Stop use and ask a doctor if

- redness is present or irritation or rash develops
- condition worsens or symptoms persist for more than 7 days
- symptoms clear up and occur again within a few days

PREGNANCY OR BREAST FEEDING

If pregnant or breast feeding, ask a healthcare professional before use

Keep out of reach of children.

If swallowed get medical help or contact a Poison Control Center immediately

Directions

- adults and children 12 years of age and older:
- rub well on the affected area. Repeat 3 to 4 times daily.
- children under 12 years of age: consult a doctor

Other information

- store at room temperature 20-25°C (68-77°F)

Inactive ingredients

clove oil, paraffin, peppermint oil, petrolatum

DOSAGE AND ADMINISTRATION

Distributed by:

United Exchange Corp.

Cypress, CA 90630 USA

1-888-645-8204

Made in China